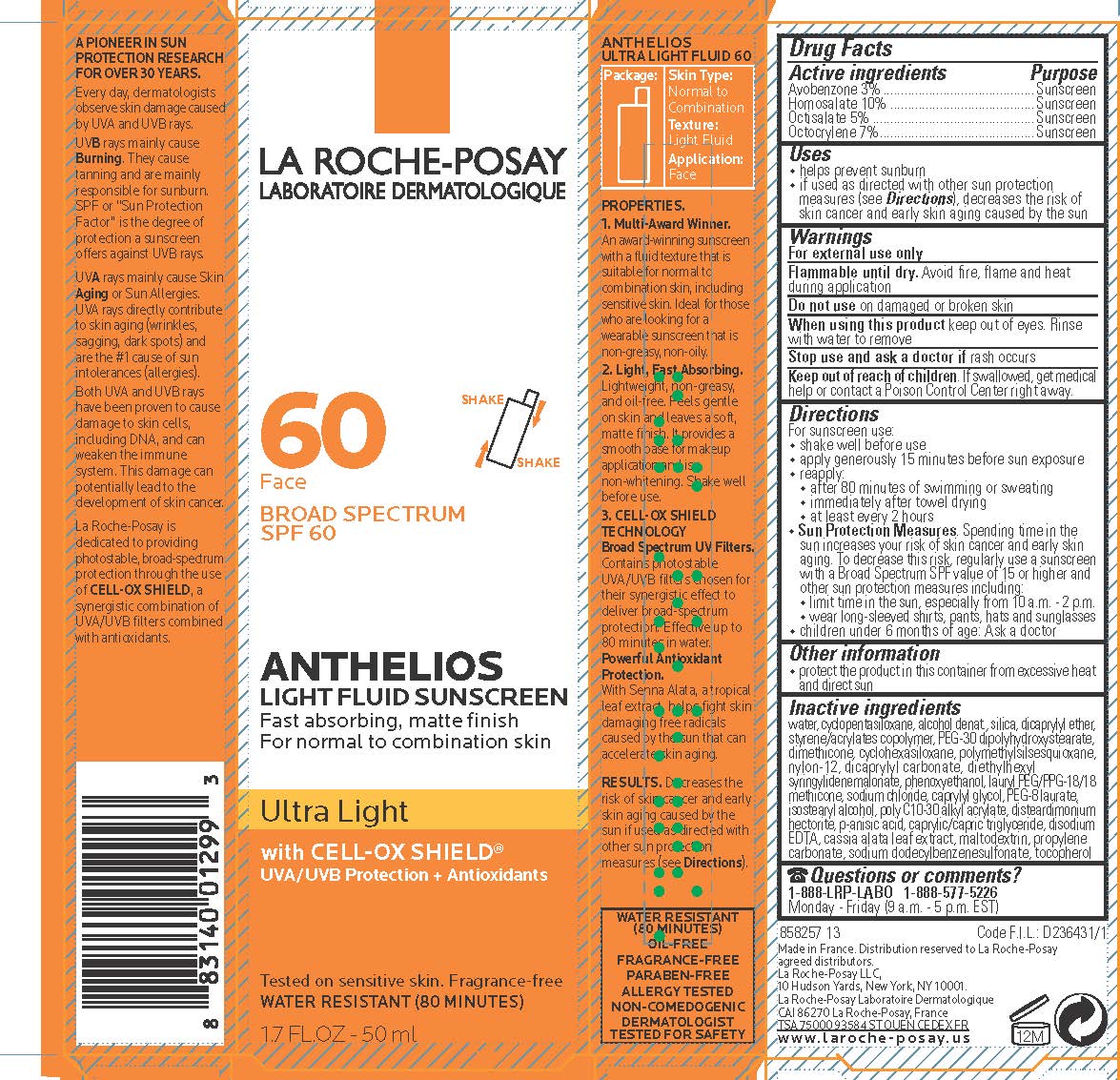 DRUG LABEL: La Roche Posay Laboratoire Dermatologique Anthelios 60 Face Light Fluid Sunscreen Broad Spectrum SPF 60 Water Resistant 80 Minutes
NDC: 69625-496 | Form: LOTION
Manufacturer: Cosmetique Active Production
Category: otc | Type: HUMAN OTC DRUG LABEL
Date: 20240131

ACTIVE INGREDIENTS: AVOBENZONE 30 mg/1 mL; HOMOSALATE 100 mg/1 mL; OCTISALATE 50 mg/1 mL; OCTOCRYLENE 70 mg/1 mL
INACTIVE INGREDIENTS: WATER; DIMETHICONE CROSSPOLYMER (450000 MPA.S AT 12% IN CYCLOPENTASILOXANE); ALCOHOL; SILICON DIOXIDE; DICAPRYLYL ETHER; STYRENE/ACRYLAMIDE COPOLYMER (MW 500000); PEG-30 DIPOLYHYDROXYSTEARATE; DIMETHICONE; CYCLOMETHICONE 6; POLYMETHYLSILSESQUIOXANE (11 MICRONS); NYLON-12; DICAPRYLYL CARBONATE; DIETHYLHEXYL SYRINGYLIDENEMALONATE; PHENOXYETHANOL; LAURYL PEG/PPG-18/18 METHICONE; SODIUM CHLORIDE; CAPRYLYL GLYCOL; PEG-8 LAURATE; ISOSTEARYL ALCOHOL; STEARYL ACRYLATE POLYMER (110000 MW); DISTEARDIMONIUM HECTORITE; P-ANISIC ACID; MEDIUM-CHAIN TRIGLYCERIDES; EDETATE DISODIUM ANHYDROUS; SENNA ALATA LEAF; MALTODEXTRIN; PROPYLENE CARBONATE; SODIUM DODECYLBENZENESULFONATE; TOCOPHEROL

Drug Facts

Active ingredients

Avobenzone 3%

Homosalate 10%

Octisalate 5%

Octocrylene 7%

Purpose

Sunscreen

Uses

- helps prevent sunburn

- if used as directed with other sun protection measures (see Directions), decreases the risk of skin cancer and early skin aging caused by the sun

Warnings

For external use only

Flammable until dry.

Avoid fire, flame and heat during application.

Do not use

on damaged or broken skin

When using this product

keep out of eyes. Rinse with water to remove.

Stop use and ask a doctor if

rash occurs

Keep out of reach of children.

If swallowed, get medical help or contact a Poison Control Center right away.

Directions

For sunscreen use:

- shake well before use
- apply generously 15 minutes before sun exposure
- reapply:

● after 80 minutes of swimming or sweating
● immediately after towel drying
● at least every 2 hours

- Sun Protection Measures. Spending time in the sun increases your risk of skin cancer and early skin aging. To decrease this risk, regularly use a sunscreen with a Broad Spectrum SPF value of 15 or higher and other sun protection measures including:

● limit time in the sun, especially from 10 a.m. – 2 p.m.
● wear long-sleeved shirts, pants, hats, and sunglasses

- children under 6 months of age: Ask a doctor

Other information

protect the product in this container from excessive heat and direct sun

Inactive ingredients

water, cyclopentasiloxane, alcohol denat., silica, dicaprylyl ether, styrene/acrylates copolymer, PEG-30 dipolyhydroxystearate, dimethicone, cyclohexasiloxane, polymethylsilsesquioxane, nylon-12, dicaprylyl carbonate, diethylhexyl syringlyidenemalonate, phenoxyethanol, lauryl PEG/PPG-18/18 methicone, sodium chloride, caprylyl glycol, PEG-8 laurate, isostearyl alcohol, poly C10-30 alkyl acrylate, disteardimonium hectorite, p-anisic acid, caprylic/capric triglyceride, disodium EDTA, cassia alata leaf extract, maltodextrin, propylene carbonate, sodium dodecylbenzenesulfonate, tocopherol

Questions or comments?

1-888-LRP-LABO 1-888-577-5226

Monday - Friday (9 a.m. - 5 p.m. EST)